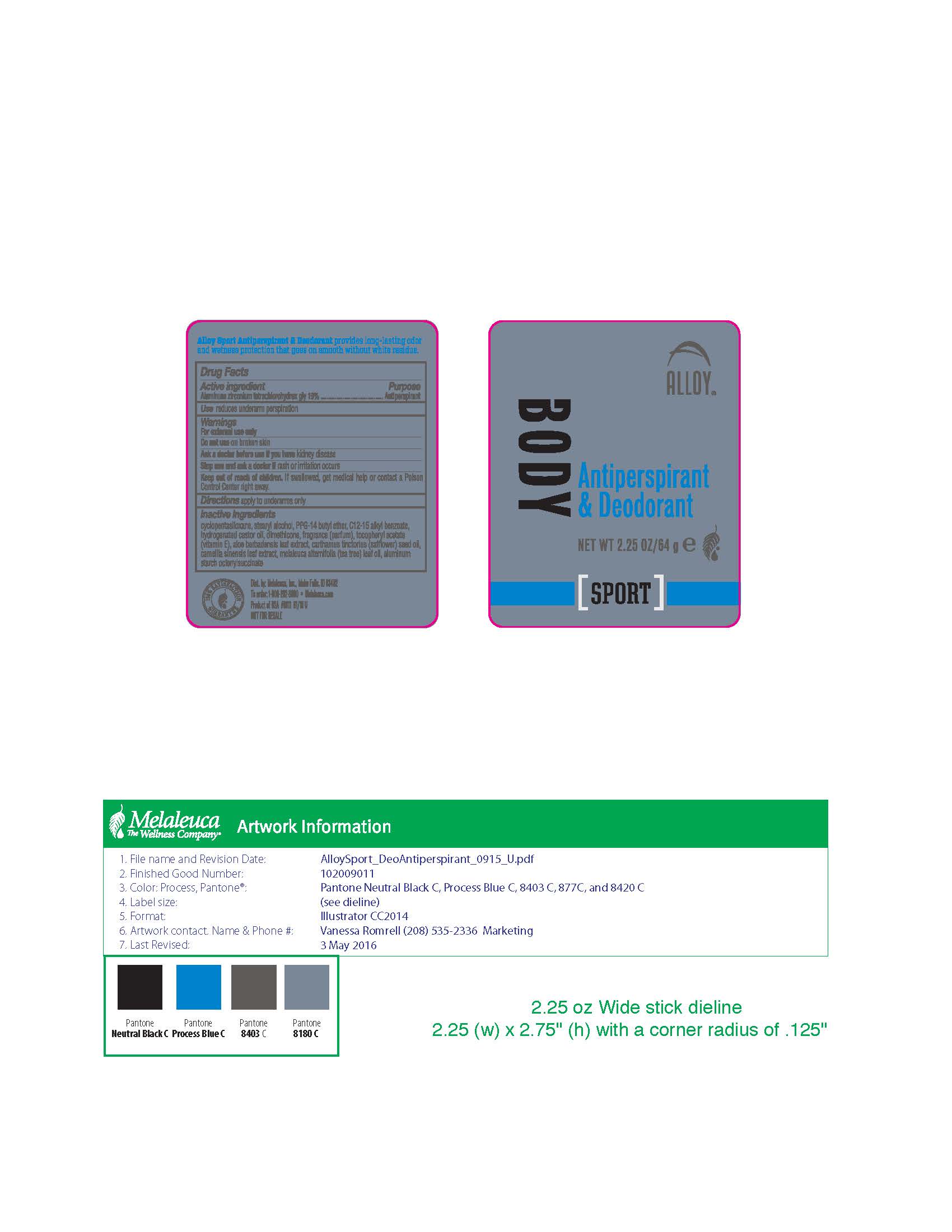 DRUG LABEL: Alloy
NDC: 54473-272 | Form: STICK
Manufacturer: Melaleuca, Inc
Category: otc | Type: HUMAN OTC DRUG LABEL
Date: 20230104

ACTIVE INGREDIENTS: ALUMINUM ZIRCONIUM TETRACHLOROHYDREX GLY 11.39 g/64 g
INACTIVE INGREDIENTS: ALOE VERA LEAF; GREEN TEA LEAF; CYCLOMETHICONE 5; HYDROGENATED CASTOR OIL; PEG-8 DISTEARATE; PPG-14 BUTYL ETHER; SODIUM BICARBONATE; STEARYL ALCOHOL; TALC; ALPHA-TOCOPHEROL ACETATE; STARCH, CORN

Alloy Sport Antiperspirant & Deodorant

Active ingredient
Aluminum zirconium tetrachlorohydrex-gly 17.8%

Purpose
Antiperspirant

INDICATIONS AND USAGE

Use reduces underarm perspiration

Warnings
For external use only

Do not use on broken skin

Ask a doctor before use if you have kidney disease

Stop use and ask a doctor if rash or irritation occurs

Keep out of reach of children. If swallowed, get medical help or contact a Poison Control Center right away.

Directions

- turn dial to raise product
- apply 2 - 3 passes to underarms only

Other information do not freeze or store above 115°F (46°C)

Inactive ingredients
Aloe barbadensis leaf juice, Camellia sinensis leaf extract, cyclopentasiloxane, fragrance, hydrogenated castor oil, PEG-8 distearate, PPG-14 butyl ether, sodium bicarbonate, stearyl alcohol, talc, tocopherol, Zea mays (corn) starch